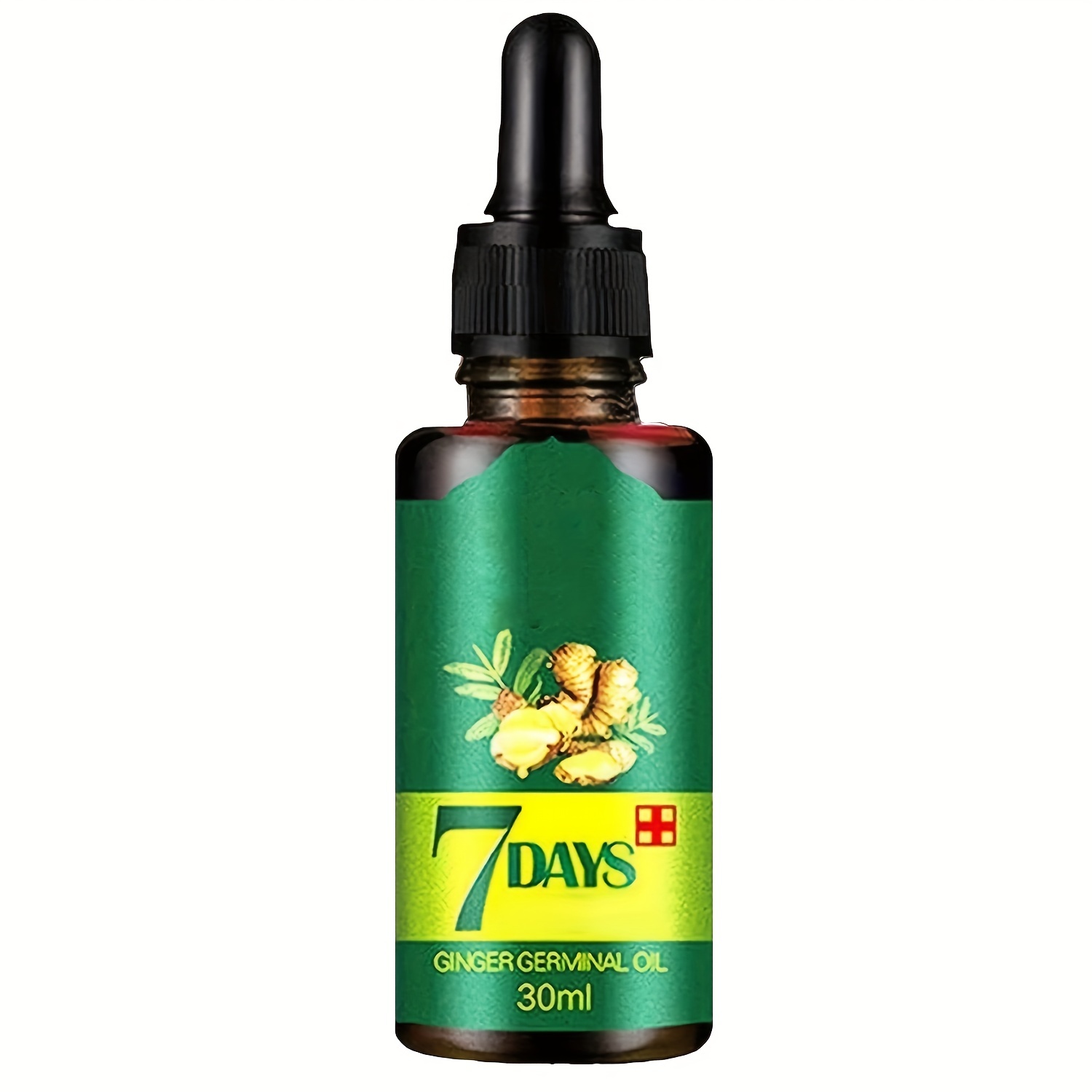 DRUG LABEL: AnYi Beauty 7 Days Ginger Germinal Oil
NDC: 84037-0034 | Form: LIQUID
Manufacturer: Guangzhou Zhicunxiu Cosmetics Co., Ltd
Category: otc | Type: HUMAN OTC DRUG LABEL
Date: 20240429

ACTIVE INGREDIENTS: NIACINAMIDE 1.8 g/45 mL; ADENOSINE 0.018 g/45 mL
INACTIVE INGREDIENTS: CARROT; GLYCERIN

AnYi Beauty 7 Days Ginger Germinal Oil

ACTIVE INGREDIENT

Active ingredients: Niacinamide 4.0%, Adenosine 0.04%

INACTIVE INGREDIENT

Inactive ingredients:
Daucus Carota Sativa (Carrot) Root Water, Glycerin, Butylene Glycol, Tranexamic Acid, Water, 1,2-Hexanediol, Dipropylene Glycol, Arbutin, Choleth-24, Hippophae Rhamnoides Fruit Extract, Panthenol, Daucus Carota Sativa (Carrot) Root Extract, Carbomer, Caprylyl Glycol, Tromethamine, Ethylhexylglycerin, Xanthan Gum, Melia Azadirachta Flower Extract, Dipotassium Glycyrrhizate, Disodium EDTA, Melia Azadirachta Leaf Extract, Citrus Aurantium Dulcis (Orange) Peel Oil, Curcuma Longa (Turmeric) Root Extract, Ocimum Sanctum Leaf Extract, Daucus Carota Sativa (Carrot) Extract, Boswellia Carterii Oil, Pelargonium Graveolens Flower Oil, Corallina Officinalis Extract, Vetiveria Zizanoides Root Oil, Amyris Balsamifera Bark Oil, Cyanocobalamin, Melaleuca Alternifolia (Tea Tree) Leaf Oil, Daucus Carota Sativa (Carrot) Seed Oil, Rose Flower Oil, Ascorbyl Glucoside, Glycine Max (Soybean) Oil, Beta-Carotene, Tocopherol

PURPOSE

Purpose: Skin Brightening, Anti wrinkle

WARNINGS

1. If there is any red spot, swallowing or itching by direct sunlight or if there is any other adverse effect during or after cosmetics use, consult with a doctor.
2. Refrain from using on the injured area
3. Precaution for storage and handling
a) Keep away from the hands of children
b) Keep away from direct sunlight

KEEP OUT OF REACH OF CHILDREN

Keep away from the hands of children

Uses

Helps brighten skin tone.
Helps improve wrinkle problem.

Directions

After using toner, apply proper amount along skin texture and stroke gently to absorb.
* Since it contains skin brightening active ingredient, for those who have sensitive skin, it is recommended to try on area behind ear or on arm before using.